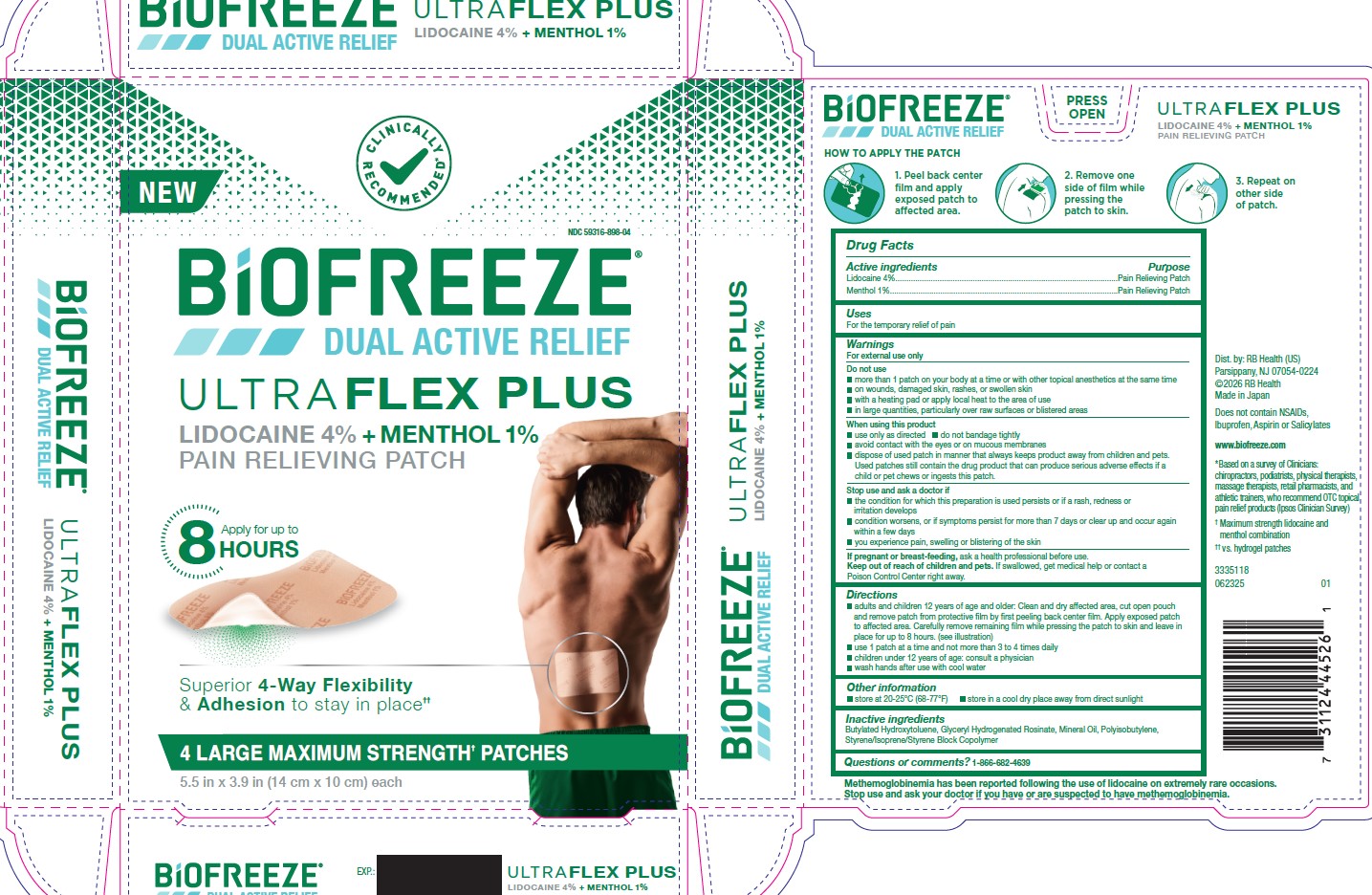 DRUG LABEL: Biofreeze Ultraflex Plus
NDC: 59316-898 | Form: PATCH
Manufacturer: RB Health (US) LLC
Category: otc | Type: HUMAN OTC DRUG LABEL
Date: 20260131

ACTIVE INGREDIENTS: MENTHOL 0.01 g/1 g; LIDOCAINE 0.04 g/1 g
INACTIVE INGREDIENTS: GLYCEROL ESTER OF HYDROGENATED ROSIN; BUTYLATED HYDROXYTOLUENE; POLYISOBUTYLENE (55000 MW); STYRENE/ISOPRENE/STYRENE BLOCK COPOLYMER; MINERAL OIL

Biofreeze Ultraflex

Active ingredient:
Lidocaine 4%

Menthol 1%

Purpose:

Pain Relieving Patch

Uses

For the temporary relief of pain

Warnings
For external use only.

Do not use
􀂄 more than 1 patch on your body at a time or with other topical anesthetics at the same time
􀂄 on wounds, damaged skin, rashes, or swollen skin
􀂄 with a heating pad or apply local heat to the area of use
􀂄 in large quantities, particularly over raw surfaces or blistered areas

When using this product
􀂄 use only as directed
􀂄 do not bandage tightly
􀂄 avoid contact with the eyes or on mucous membranes
􀂄 dispose of used patch in manner that always keeps product away from children and pets.
Used patches still contain the drug product that can produce serious adverse effects if a
child or pet chews or ingests this patch.

Stop use and ask a doctor if
􀂄 the condition for which this preparation is used persists or if a rash, redness or
irritation develops
􀂄 condition worsens, or if symptoms persist for more than 7 days or clear up and occur again
within few days
􀂄 you experience pain, swelling or blistering of the skin

If pregnant or breast-feeding, ask a health professional before use.
Keep out of reach of children and pets. If swallowed, get medical help or contact a
Poison Control Center right away.

Uses
For the temporary relief of pain

Keep out of reach of children and pets. If swallowed, get medical help or contact a
Poison Control Center right away.

Directions
􀂄 adults and children 12 years of age and older: Clean and dry affected area, cut open pouch
and remove patch from protective film by first peeling back center film. Apply exposed patch
to affected area. Carefully remove remaining film while pressing the patch to skin and leave in
place for up to 8 hours. (see images on carton)
􀂄 use 1 patch at a time and not more than 3 to 4 times daily
􀂄 children under 12 years of age: consult a physician
􀂄 wash hands after use with cool water

Other information
􀂄 store at 20-25°C (68-77°F)
􀂄 store in a cool dry place away from direct sunlight

Inactive ingredients:
Butylated Hydroxytoluene, Glyceryl Hydrogenated Rosinate, Mineral Oil, Polyisobutylene,
Styrene/Isoprene/Styrene Block Copolymer

Questions or comments? 1-866-682-4639